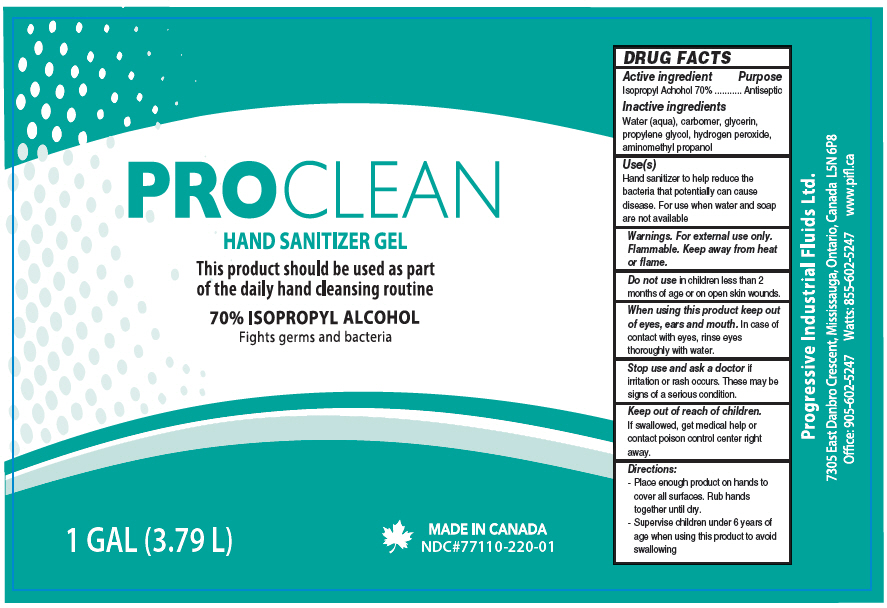 DRUG LABEL: PROCLEAN HAND SANITIZER
NDC: 77110-220 | Form: GEL
Manufacturer: Biominerales Pharma
Category: otc | Type: HUMAN OTC DRUG LABEL
Date: 20200909

ACTIVE INGREDIENTS: ISOPROPYL ALCOHOL 70 mL/100 mL
INACTIVE INGREDIENTS: WATER; CARBOMER HOMOPOLYMER, UNSPECIFIED TYPE; GLYCERIN; PROPYLENE GLYCOL; HYDROGEN PEROXIDE; AMINOMETHYLPROPANOL

PROCLEAN HAND SANITIZER

DRUG FACTS

Active ingredient

Isopropyl Achohol 70%

Purpose

Antiseptic

Inactive ingredients

Water (aqua), carbomer, glycerin, propylene glycol, hydrogen peroxide, aminomethyl propanol

Use(s)

Hand sanitizer to help reduce the bacteria that potentially can cause disease. For use when water and soap are not available

Warnings

For external use only. Flammable. Keep away from heat or flame.

Do not use in children less than 2 months of age or on open skin wounds.

When using this product keep out of eyes, ears and mouth. In case of contact with eyes, rinse eyes thoroughly with water.

Stop use and ask a doctor if irritation or rash occurs. These may be signs of a serious condition.

Keep out of reach of children. If swallowed, get medical help or contact poison control center right away.

Directions

- Place enough product on hands to cover all surfaces. Rub hands together until dry.
- Supervise children under 6 years of age when using this product to avoid swallowing

PRINCIPAL DISPLAY PANEL - 3.79 L Bottle Label

PROCLEAN

HAND SANITIZER GEL

This product should be used as part
of the daily hand cleansing routine

70% ISOPROPYL ALCOHOL
Fights germs and bacteria

1 GAL (3.79 L)

MADE IN CANADA
NDC#77110-220-01